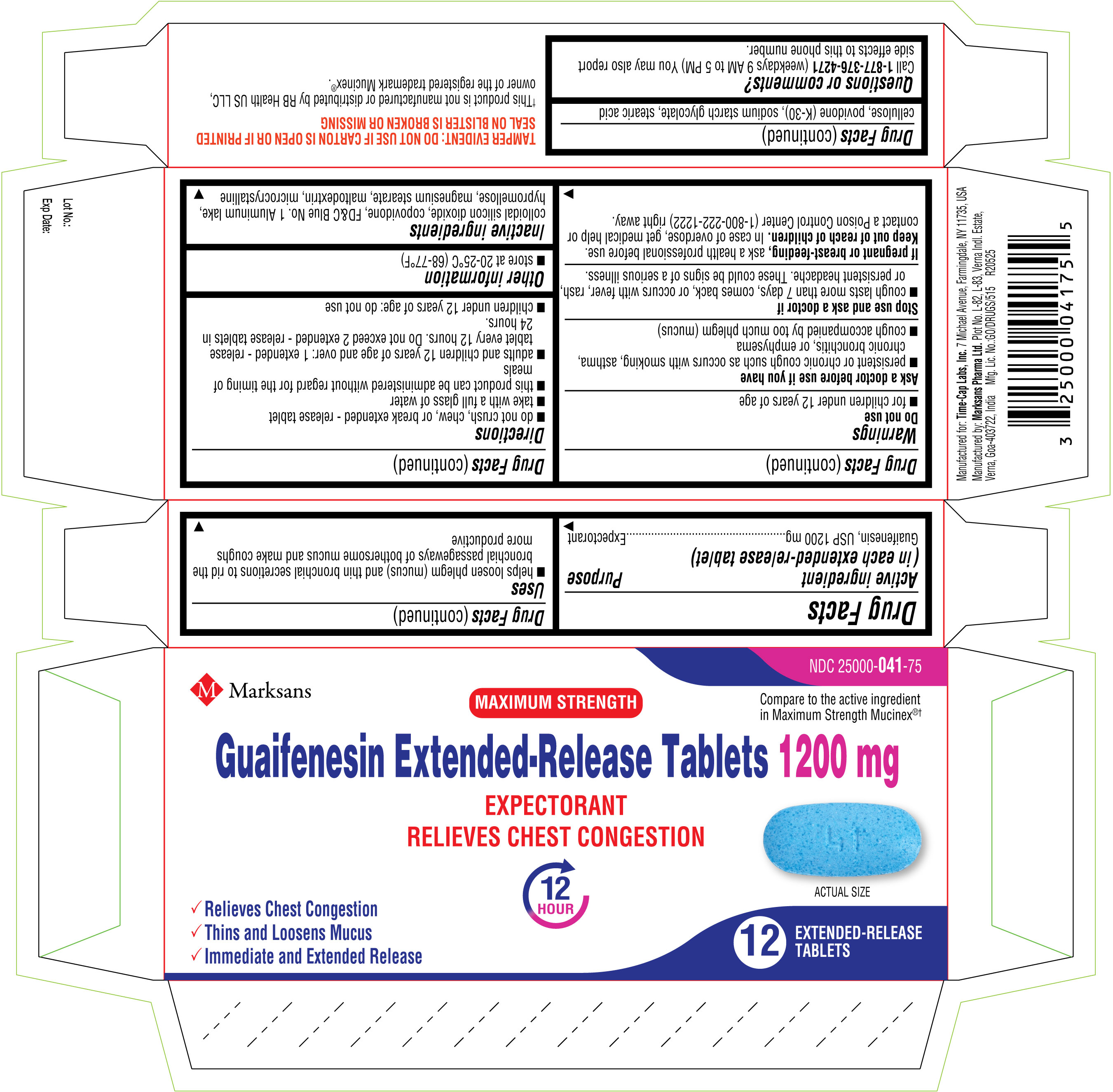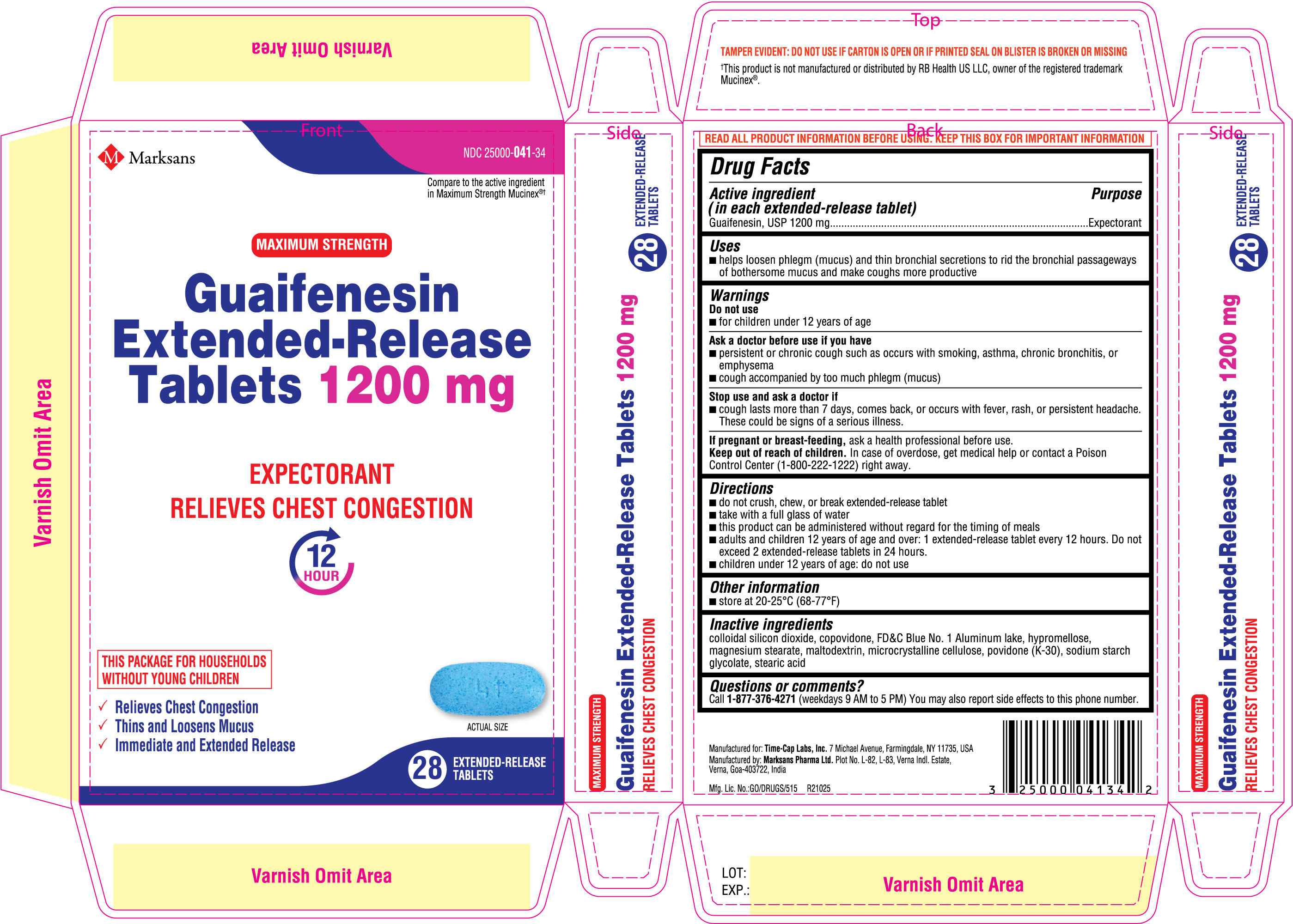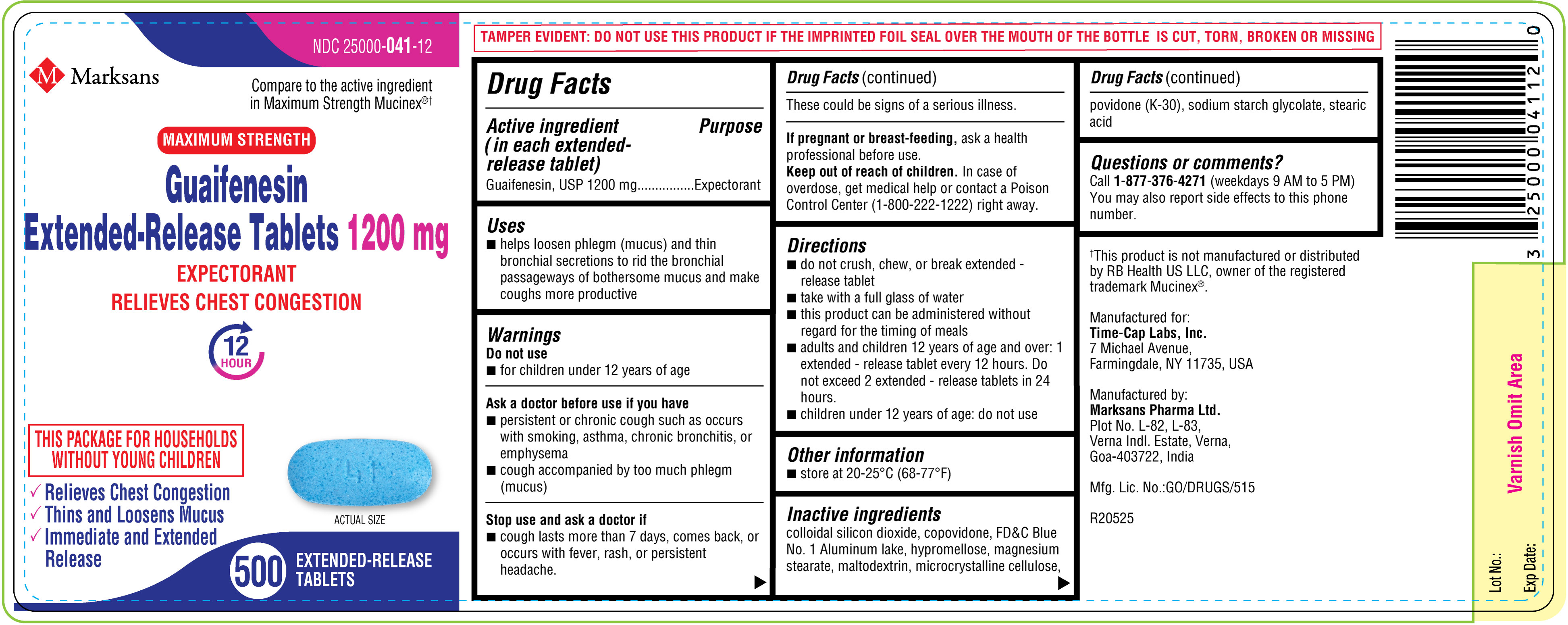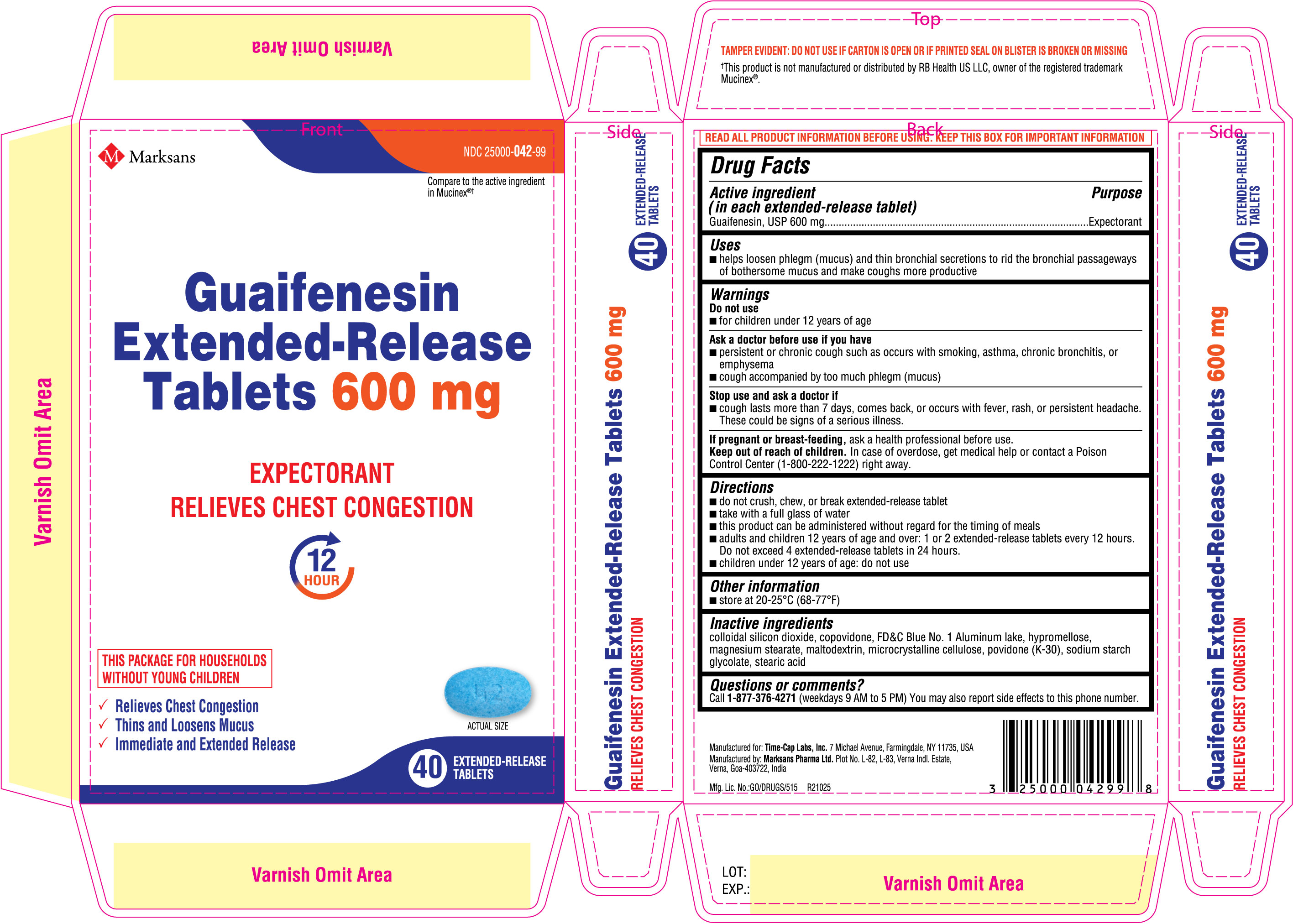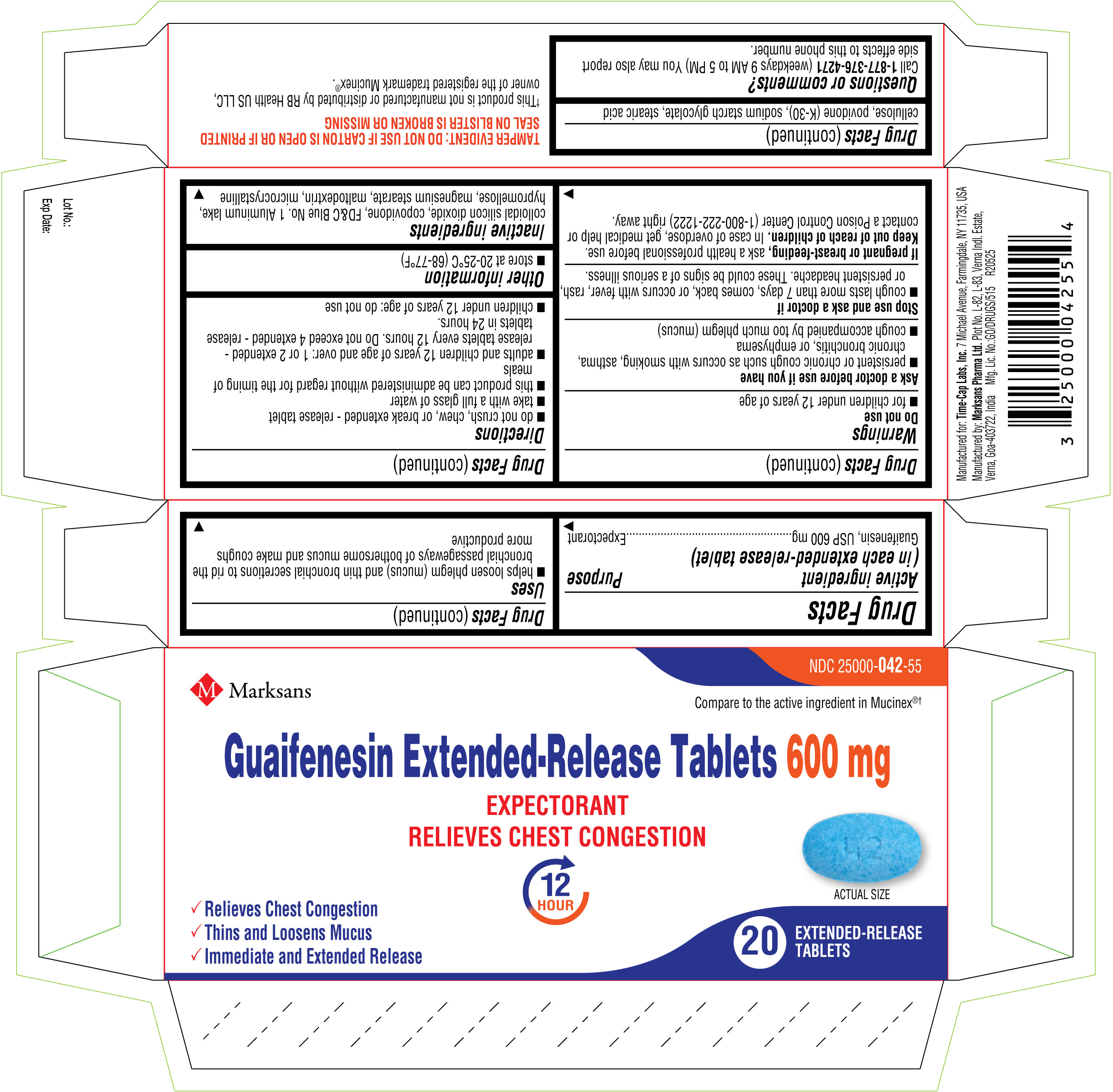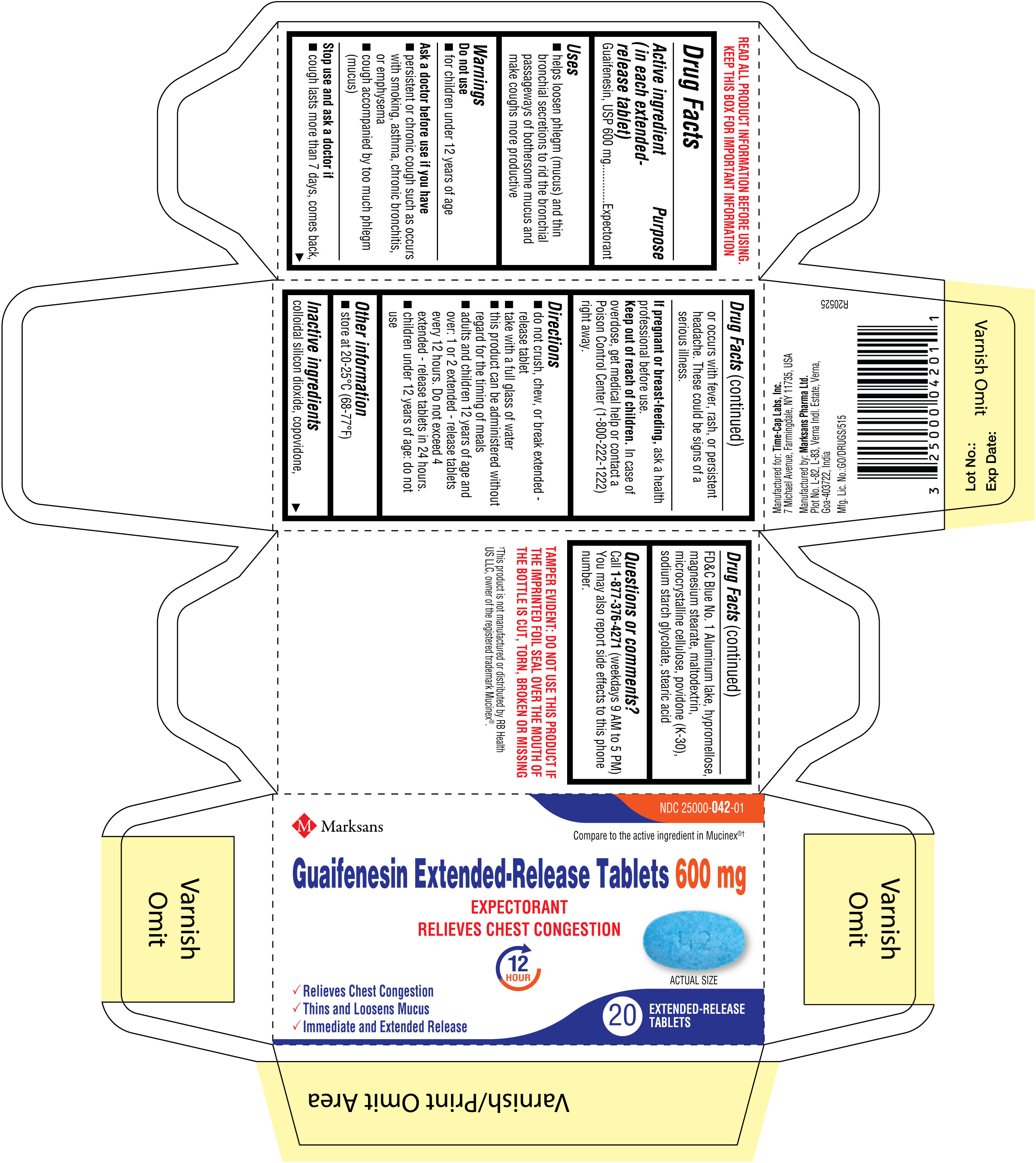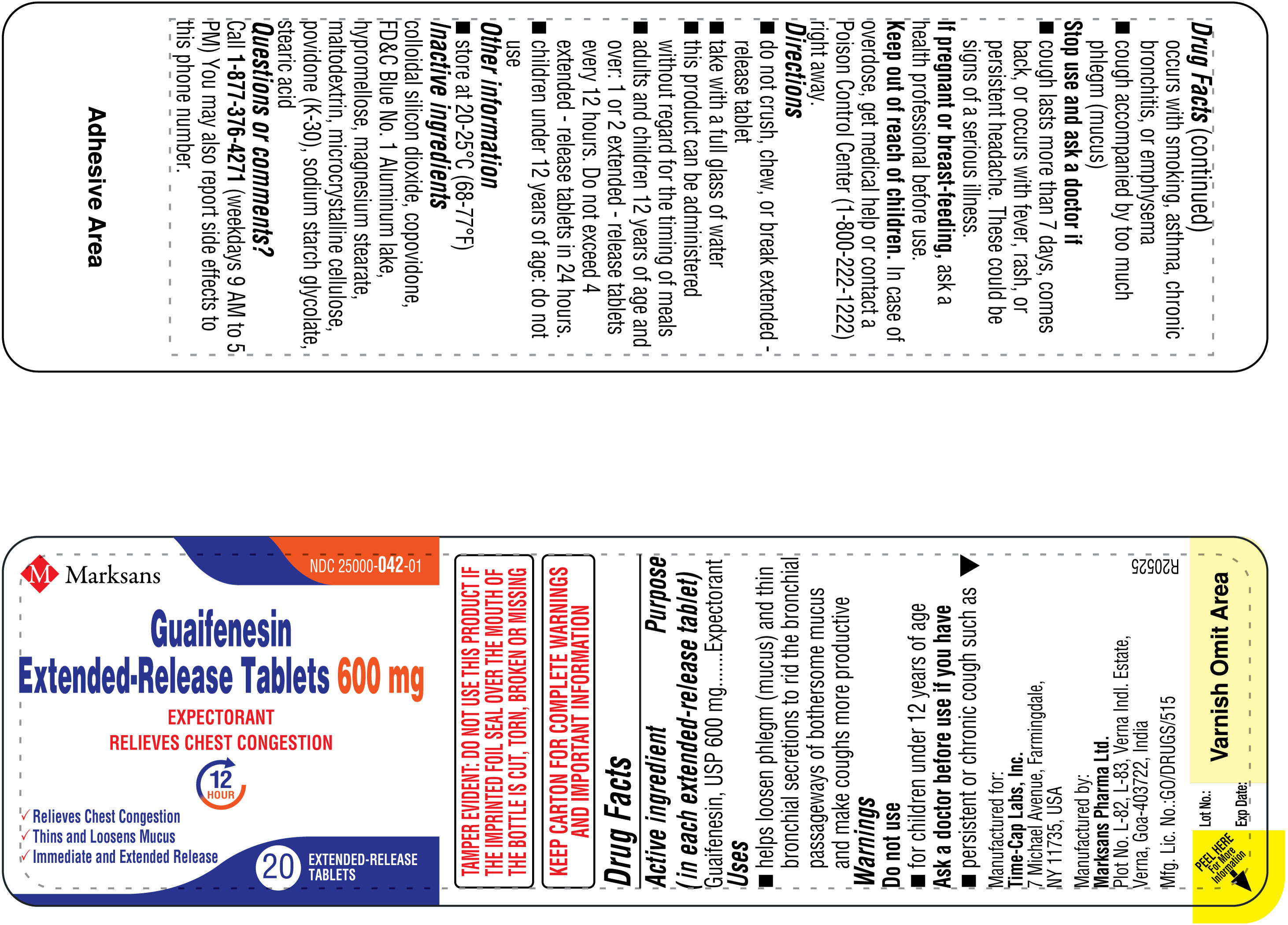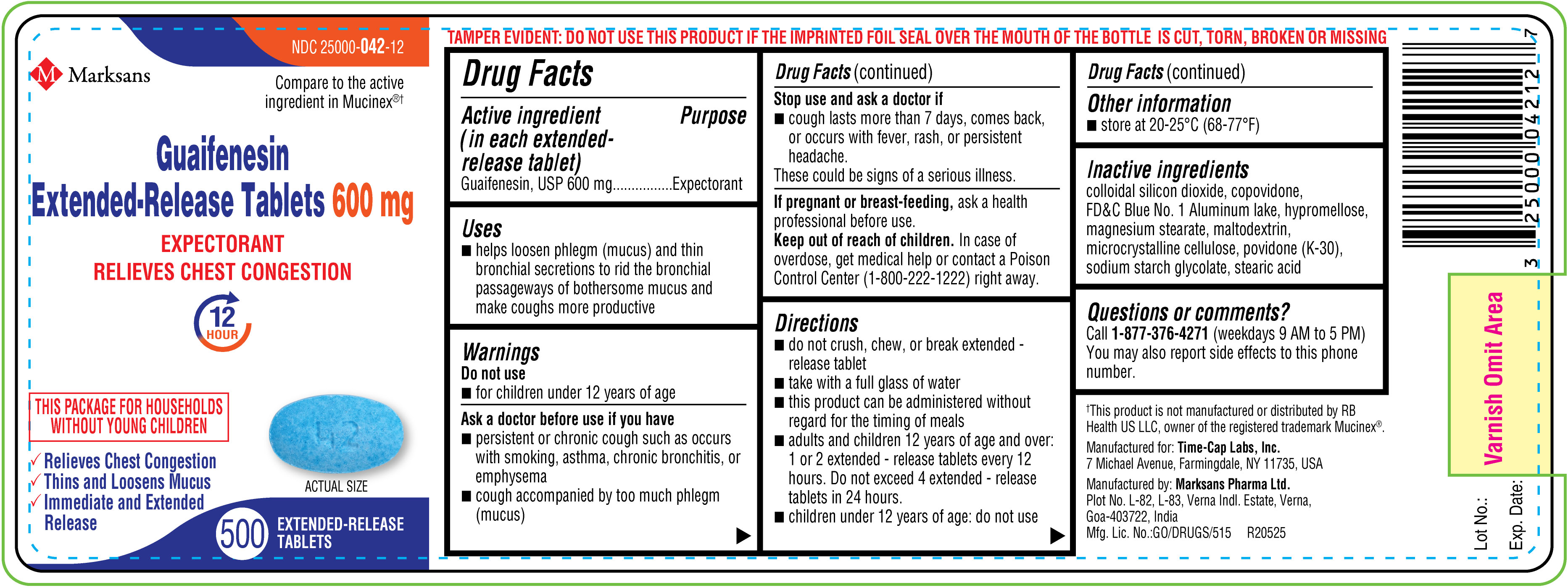 DRUG LABEL: Guaifenesin 600 mg
NDC: 25000-042 | Form: TABLET
Manufacturer: MARKSANS PHARMA LIMITED
Category: otc | Type: Human OTC Drug Label
Date: 20251017

ACTIVE INGREDIENTS: GUAIFENESIN 600 mg/1 1
INACTIVE INGREDIENTS: SILICON DIOXIDE; COPOVIDONE K25-31; HYPROMELLOSE, UNSPECIFIED; MAGNESIUM STEARATE; MALTODEXTRIN; MICROCRYSTALLINE CELLULOSE 102; POVIDONE K30; SODIUM STARCH GLYCOLATE TYPE A; STEARIC ACID; FD&C BLUE NO. 1 ALUMINUM LAKE

Guaifenesin Extended-Release Tablets 600 mg and 1200 mg

OTC - ACTIVE INGREDIENT SECTION

For 600 mg:
Active ingredient (in each extended-release tablet)

Guaifenesin, USP 600 mg

For 1200 mg:
Active ingredient (in each extended-release tablet)

Guaifenesin, USP 1200 mg

OTC - PURPOSE SECTION

Purpose

Expectorant

INDICATIONS & USAGE SECTION

Uses

• helps loosen phlegm (mucus) and thin bronchial secretions to rid the bronchial passageways of bothersome mucus and make coughs more productive

OTC - DO NOT USE SECTION

Do not use

• for children under 12 years of age

OTC - ASK DOCTOR SECTION

Ask a doctor before use if you have

• persistent or chronic cough such as occurs with smoking, asthma, chronic bronchitis, or emphysema
• cough accompanied by too much phlegm (mucus)

OTC - STOP USE SECTION

Stop use and ask a doctor if

- cough lasts more than 7 days, comes back, or occurs with fever, rash, or persistent headache. These could be signs of a serious illness.

OTC - PREGNANCY OR BREAST FEEDING SECTION

If pregnant or breast-feeding, ask a health professional before use.

OTC - KEEP OUT OF REACH OF CHILDREN SECTION

Keep out of reach of children. In case of overdose, get medical help or contact a Poison Control Center (1-800-222-1222) right away.

DOSAGE & ADMINISTRATION SECTION

Directions

For 600 mg

• do not crush, chew, or break extended - release tablet
• take with a full glass of water
• this product can be administered without regard for the timing of meals
• adults and children 12 years of age and over: 1 or 2 extended - release tablets every 12 hours. Do not exceed 4 extended - release tablets in 24 hours.
• children under 12 years of age: do not use

For 1200 mg

• do not crush, chew, or break extended - release tablet
• take with a full glass of water
• this product can be administered without regard for the timing of meals
• adults and children 12 years of age and over: 1 extended - release tablet every 12 hours. Do not exceed 2 extended - release tablets in 24 hours.
• children under 12 years of age: do not use

STORAGE AND HANDLING SECTION

Other information

• store at 20-25°C (68-77°F)

INACTIVE INGREDIENT SECTION

Inactive ingredients colloidal silicon dioxide, copovidone, FD&C Blue No. 1 Aluminum lake, hypromellose, magnesium stearate, maltodextrin, microcrystalline cellulose, povidone (K-30), sodium starch glycolate, stearic acid

OTC - QUESTIONS SECTION

Questions or comments?

Call 1-877-376-4271 (weekdays 9 AM to 5 PM)
You may also report side effects to this phone number.

Manufactured for:
Time-Cap Labs, Inc.
7 Michael Avenue,
Farmingdale,
NY 11735, USA

Manufactured by:
Marksans Pharma Ltd.
Plot No. L-82, L-83
Verna Indl. Estate
Verna, Goa-403722, India

PRINCIPAL DISPLAY PANEL

NDC: 25000-042-55
Guaifenesin Extended-Release Tablets 600 mg
20's count (2 x 10's blister) Carton

NDC: 25000-042-01

Guaifenesin Extended-Release Tablets 600 mg

20's count Bottle Label

NDC: 25000-042-01

Guaifenesin Extended-Release Tablets 600 mg

20's count Bottle Carton

NDC: 25000-042-12
Guaifenesin Extended-Release Tablets 600 mg
500's count Bottle Label

NDC: 25000-042-99

Guaifenesin Extended-Release Tablets 600 mg

40's count (2 x 20's blister) Carton

NDC: 25000-041-75
Guaifenesin Extended-Release Tablets 1200 mg
12's count (2 x 6's blister) Carton

NDC: 25000-041-12
Guaifenesin Extended-Release Tablets 1200 mg
500's count Bottle Label

NDC: 25000-041-34

Guaifenesin Extended-Release Tablets 1200 mg

28's count (2 x 14's blister) Carton